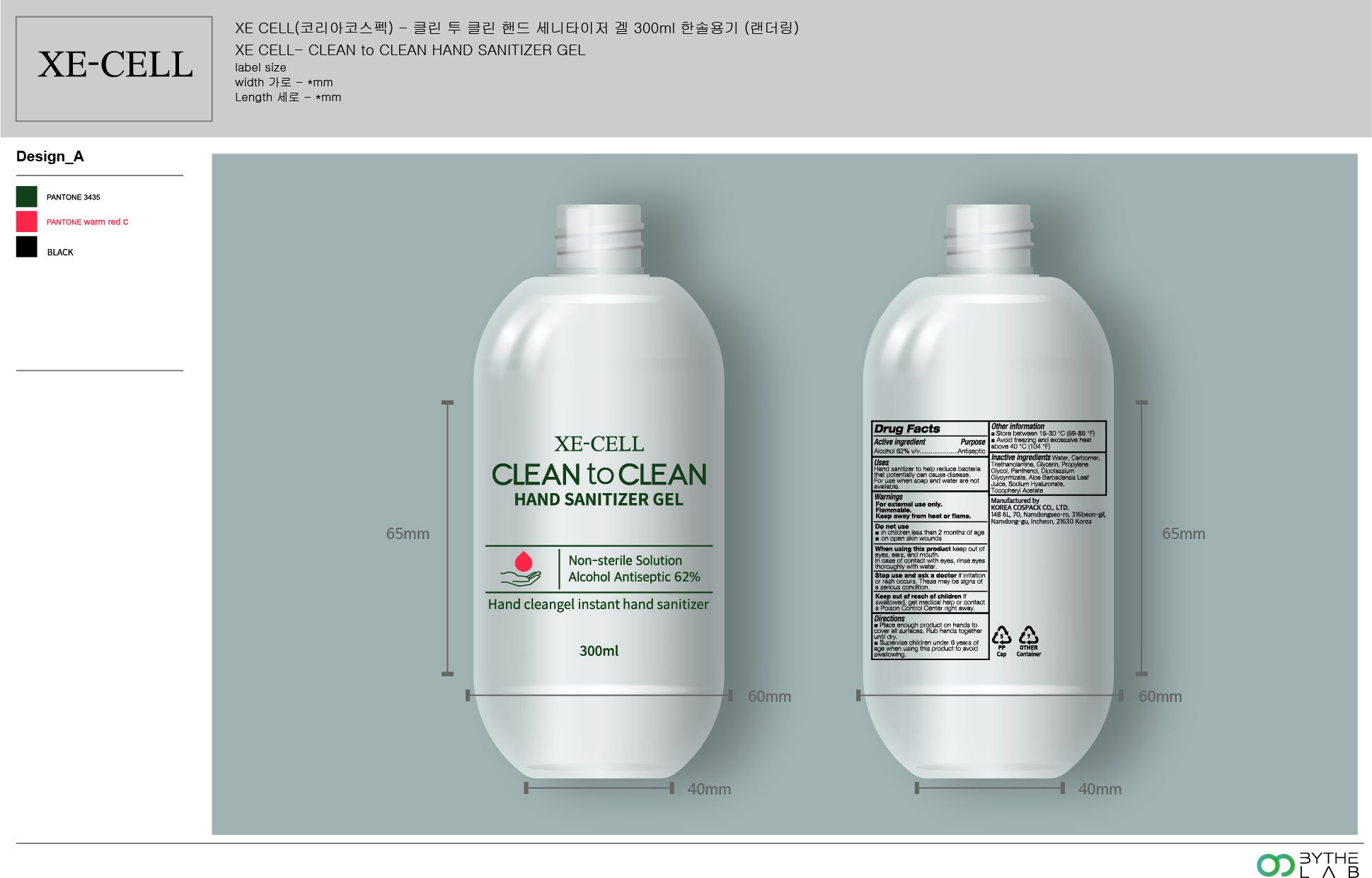 DRUG LABEL: CLEAN TO CLEAN HAND SANITIZER Gel
NDC: 74064-2362 | Form: GEL
Manufacturer: KOREA COSPACK CO.,LTD.
Category: otc | Type: HUMAN OTC DRUG LABEL
Date: 20200411

ACTIVE INGREDIENTS: ALCOHOL 186 mL/300 mL
INACTIVE INGREDIENTS: GLYCERIN; CARBOMER HOMOPOLYMER, UNSPECIFIED TYPE; WATER; PROPYLENE GLYCOL; PANTHENOL; GLYCYRRHIZINATE DIPOTASSIUM; ALOE VERA LEAF; .ALPHA.-TOCOPHEROL ACETATE; HYALURONATE SODIUM; TROLAMINE

[CLEAN TO CLEAN HAND SANITIZER Gel] 300 ml -2 : 74064-2362